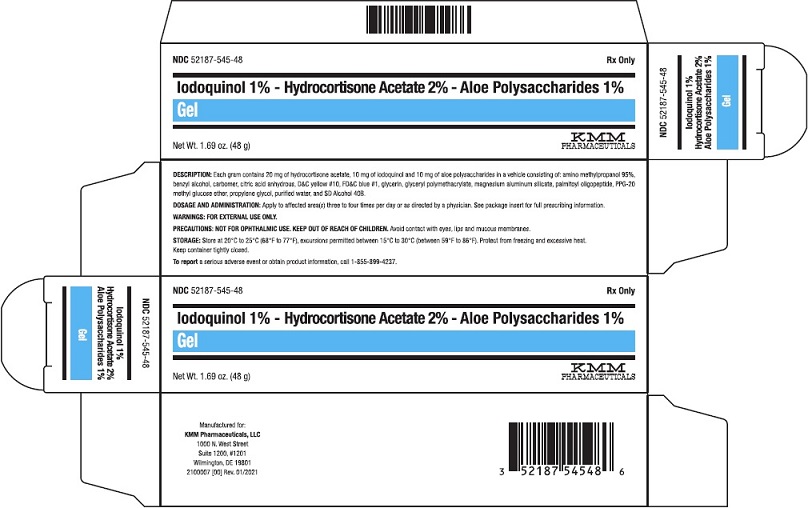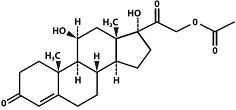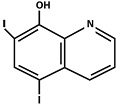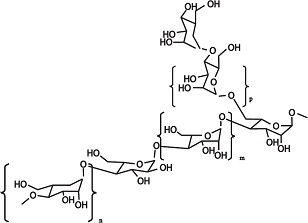 DRUG LABEL: IODOQUINOL, HYDROCORTISONE ACETATE, ALOE POLYSACCHARIDES
NDC: 52187-545 | Form: GEL
Manufacturer: KMM Pharmaceuticals, LLC
Category: prescription | Type: HUMAN PRESCRIPTION DRUG LABEL
Date: 20241104

ACTIVE INGREDIENTS: ALOE VERA LEAF POLYSACCHARIDES 10 mg/1 g; HYDROCORTISONE ACETATE 20 mg/1 g; IODOQUINOL 10 mg/1 g

Iodoquinol 1% Hydrocortisone Acetate 2% Aloe Polysaccharides 1% Gel

Iodoquinol 1% Hydrocortisone Acetate 2% Aloe Polysaccharides 1% Gel

Rx Only

DESCRIPTION:

Each gram contains 20 mg of hydrocortisone acetate, 10 mg of iodoquinol and 10 mg of aloe polysaccharides in a vehicle consisting of: amino methylpropanol 95%, benzyl alcohol, carbomer, citric acid anhydrous, D&C yellow #10, FD&C blue #1, glycerin, glyceryl polymethacrylate, magnesium aluminum silicate, palmitoyl oligopeptide, PPG-20 methyl glucose ether, propylene glycol, purified water, and SD Alcohol 40B.

Hydrocortisone acetate is an anti-inflammatory and antipruritic agent. Chemically, hydrocortisone acetate is [Pregn-4-ene-3, 20-dione, 21-(acetyloxy)-11, 17-dihydroxy-, (11-ß)-] with the molecular formula (C23H32O6) and is represented by the following structural formula:

Iodoquinol is an antifungal and antibacterial agent. Chemically, Iodoquinol is [5,7-diiodo-8-quinolinol] with the molecular formula (C9H5I2NO) and is represented by the following structural formula:

Aloe polysaccharides are a concentrated, water soluble subcomponent of aloe vera with a mono-sugar ratio of Man : Gal : Glc: 40 : 1.4 : 1.0, linkage of 1-4 ß - linkage, O-Acetyl group of 25% of sugar units, and specific rotation of [α]D= -3.98° at 23.2°C. Average molecular weight is 80,000 daltons. Chemically, aloe polysaccharides is represented by the following structural formula:

CLINICAL PHARMACOLOGY:

Hydrocortisone acetate has anti-inflammatory, antipruritic and vasoconstrictive properties. While the mechanism of anti-inflammatory activity is unclear, there is evidence to suggest that a recognizable correlation exists between vasoconstrictor potency and therapeutic efficacy in humans. Iodoquinol has both antifungal and antibacterial properties.

Pharmacokinetics: The extent of percutaneous absorption of topical steroids is determined by many factors including the vehicle, the integrity of the epidermal barrier and the use of occlusive dressings. Hydrocortisone acetate can be absorbed from normal intact skin. Inflammation and/or other inflammatory disease processes in the skin increase percutaneous absorption. Occlusive dressings substantially increase the percutaneous absorption of topical corticosteroids. Once absorbed through the skin, hydrocortisone acetate is metabolized in the liver and most body tissue to hydrogenated and degraded forms such as tetrahydrocortisone and tetrahydrocortisol. These are excreted in the urine, mainly conjugated as glucuronides, together with a very small proportion of unchanged hydrocortisone acetate. There are no data available regarding the percutaneous absorption of iodoquinol; however, following oral administration, 3-5% of the dose was recovered in the urine as a glucuronide.

INDICATIONS:

Based on a review of a related drug by the National Research Council and subsequent FDA classification for that drug, the indications are as follows: “Possibly” Effective: Contact or atopic dermatitis; impetiginized eczema; nummular eczema; endogenous chronic infectious dermatitis; stasis dermatitis; pyoderma; nuchal eczema and chronic eczematoid otitis externa; acne urticata; localized or disseminated neurodermatitis; lichen simplex chronicus; anogenital pruritus (vulvae, scroti, ani); folliculitis; bacterial dermatoses; mycotic dermatoses such as tinea (capitis, cruris, corporis, pedis); monliasis; intertrigo. Final classification of the less-than-effective indications requires further investigation.

CONTRAINDICATIONS:

This product is contraindicated in persons with known or suspected hypersensitivity to any of the ingredients of the product.

WARNINGS:

KEEP OUT OF REACH OF CHILDREN.

PRECAUTIONS:

FOR EXTERNAL USE ONLY. NOT FOR OPHTHALMIC USE. Avoid contact with eyes, lips and mucous membranes.

Information for Patients: If irritation develops, the use of this product should be discontinued and appropriate therapy instituted. Staining of the skin, hair and fabrics may occur. Not intended for use on infants or under diapers or occlusive dressings. If extensive areas are treated or if the occlusive dressing technique is used, the possibility exists of increased systemic absorption of the corticosteroid, and suitable precautions should be taken. Children may absorb proportionally larger amounts of topical corticosteroids and thus be more susceptible to systemic toxicity. Parents of pediatric patients should be advised not to use tight-fitting diapers or plastic pants on a child being treated in the diaper area, as these garments may constitute occlusive dressings.

Iodoquinol may be absorbed through the skin and interfere with thyroid function tests. If such tests are contemplated, wait at least one month after discontinuance of therapy to perform these tests. The ferric chloride test for phenylketonuria (PKU) can yield a false positive result if iodoquinol is present in the diaper or urine. Prolonged use may result in overgrowth of non-susceptible organisms requiring appropriate therapy.

Carcinogenesis, Mutagenesis and Impairment of Fertility: Long-term animal studies for carcinogenic potential have not been performed on this product to date. In vitro studies to determine mutagenicity with hydrocortisone have revealed negative results. Mutagenicity studies have not been performed with iodoquinol.

Pregnancy: Category C. Animal reproduction studies have not been conducted with this product. It is also not known whether this product can affect reproduction capacity or cause fetal harm when administered to a pregnant woman. This product should be used by a pregnant woman only if clearly needed or when potential benefits outweigh potential hazards to the fetus.

Nursing Mothers: It is not known whether this drug is excreted in human milk. Because many drugs are excreted in human milk, caution should be exercised when this product is administered to a nursing woman.

Pediatric Use: Safety and effectiveness in pediatric patients under the age of 12 have not been established.

ADVERSE REACTIONS:

The following local adverse reactions are reported infrequently with topical corticosteroids. These reactions are listed in an approximate decreasing order of occurrence: burning, itching, irritation, dryness, folliculitis, hypertrichosis, acneiform eruptions, hypopigmentation, perioral dermatitis, allergic contact dermatitis, maceration of the skin, secondary infections, skin atrophy, striae and miliaria.

DOSAGE AND ADMINISTRATION:

Apply to affected area(s) three to four times per day or as directed by a physician. Follow your physician’s directions regarding length of treatment after symptoms resolve.

STORAGE:

Store at 20°C to 25°C (68°F to 77°F), excursions permitted between 15°C to 30°C (between 59°F to 86°F). Brief exposure to temperatures up to 40°C (104°F) may be tolerated provided the mean kinetic temperature does not exceed 25°C (77°F); however, such exposure should be minimized. Keep container tightly closed.

NOTICE: Protect from freezing and excessive heat.

HOW SUPPLIED:

1.69 oz. (48 g) tube, NDC 52187-545-48

To report a serious adverse event or obtain product information, call 1-855-899-4237.

Manufactured for:

KMM Pharmaceuticals, LLC

1000 N. West Street

Suite 1200, #1201

Wilmington, DE 19801

2100006 [00] Rev. 01/2021